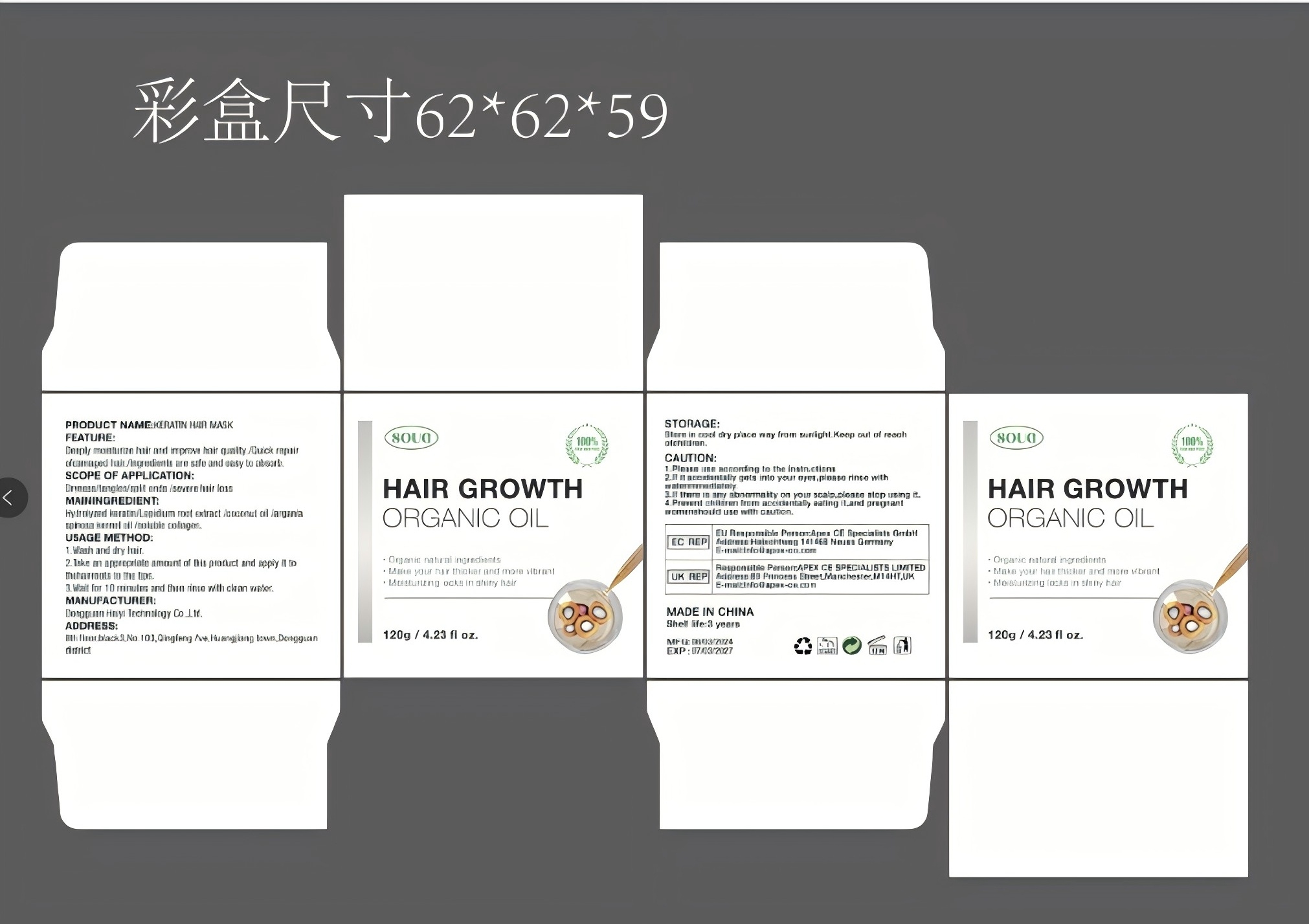 DRUG LABEL: SY Bata Hair Oil
NDC: 84778-023 | Form: CREAM
Manufacturer: Guangzhou Yixin Cross-border E-commerce Co., Ltd.
Category: otc | Type: HUMAN OTC DRUG LABEL
Date: 20241104

ACTIVE INGREDIENTS: ELAEIS OLEIFERA SEED OIL 10 g/10 g

COMPONENTS

Elaeis Oleifera Kernel Oil 10g

PURPOSE

Hair care solutions for thicker, stronger, smoother and more hydrating hair

INDICATIONS AND USAGE

Promotes healthy hair growth, making hair healthier, smoother and more manageable

WARNINGS

For external use only, please avoid contact with eyes. If it gets into eyes accidentally, rinse with clean water immediately.
It is recommended to perform a skin test on the inside of the wrist before use. If allergic reactions such as redness, swelling, itching, etc. occur, please stop using it immediately.

DOSAGE AND ADMINISTRATION

For external use only.

DO NOT USE

Skin: Do not use on wounds, inflammation or infected skin.
Around the eyes: Avoid applying hair oil directly to the eyes and the area around the eyes, which may cause irritation.
Adhesive membrane area: Do not use in the mouth, nose and other areas of the adhesive membrane.
Sensitive skin: People who are sensitive to plant ingredients or have a history of allergies should use it strictly, and it is best to conduct an allergy test first.
Use on wet hair: Try to avoid using it on wet hair, which will seriously affect the absorption effect of the product.

WHEN USING

Sensitive skin: People who are sensitive to plant ingredients or have a history of allergies should use it strictly, and it is best to conduct an allergy test first.

STOP USE

Allergic reaction: If you experience redness, itching, stinging or other discomfort during use, please stop using it immediately.

Irritation: If you feel persistent stinging or burning sensation on your scalp or skin, stop using it immediately and rinse with water.

No obvious effect: If you do not see obvious improvement or effect after continuous use, it is recommended to stop using it and consider consulting a professional.

Injury or infection: If you have a wound, infection or other skin problem on your scalp, you should stop using it and seek medical advice.

Pregnancy or constipation: If you feel uncomfortable during pregnancy or constipation, it is recommended to stop using it and consult a doctor.

Keep out of reach of children and pets.

Do not use this box incribs,beds,carriages or play pens,This Product is not a TOY.

INACTIVE INGREDIENT

HydrolyzedKeratin
ScutellariaBaicalensisRootExtract
CocosNucifera(Coconut)Oil
SolubleCollagen
SnakeOil